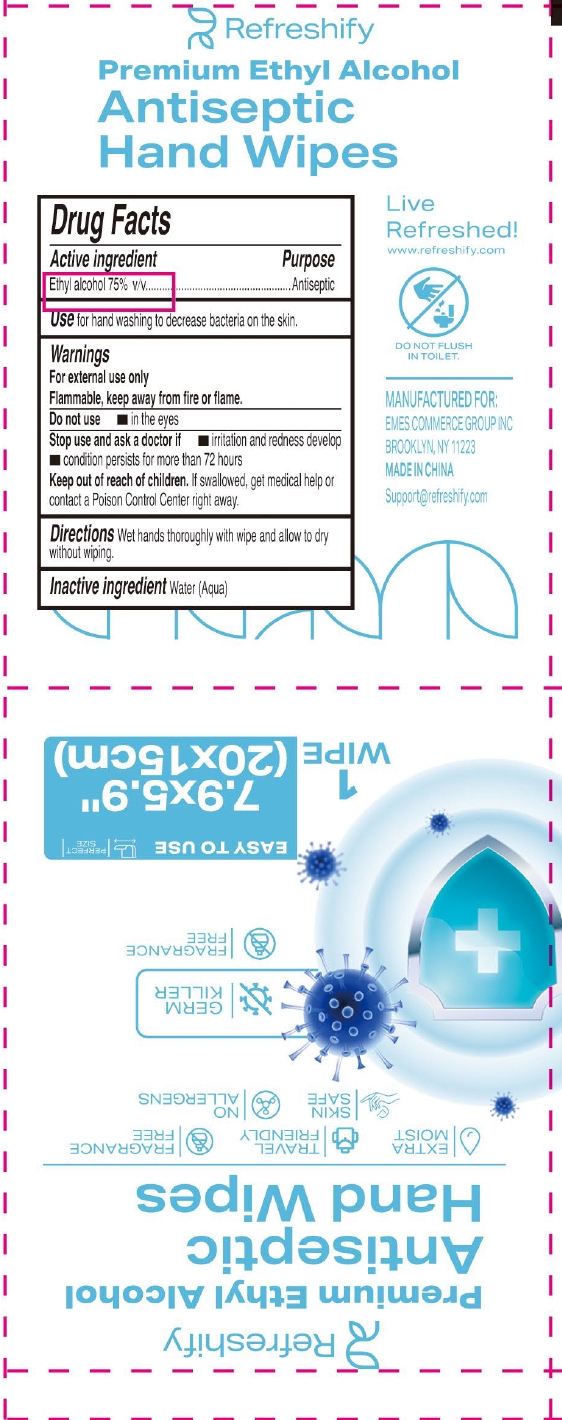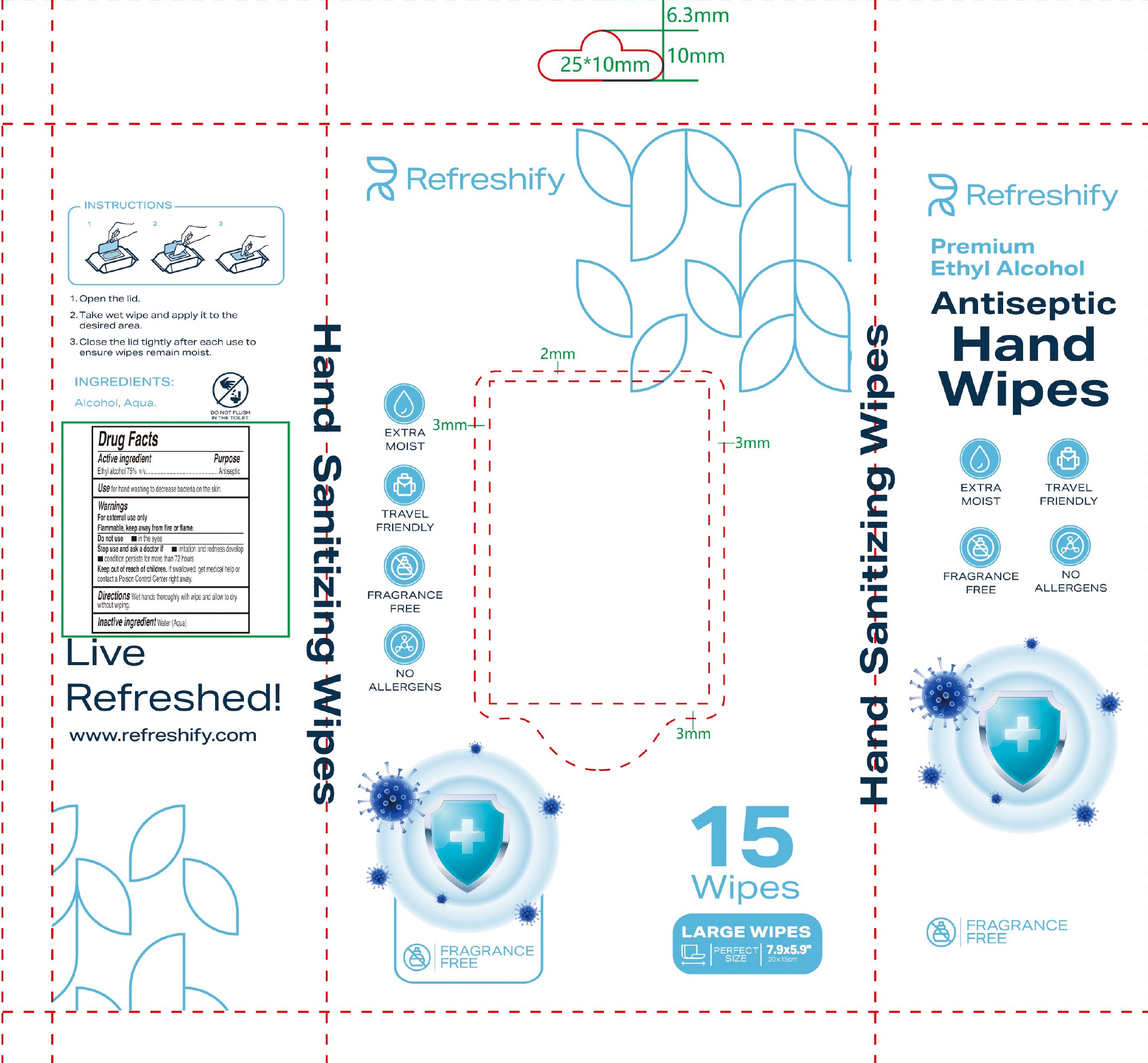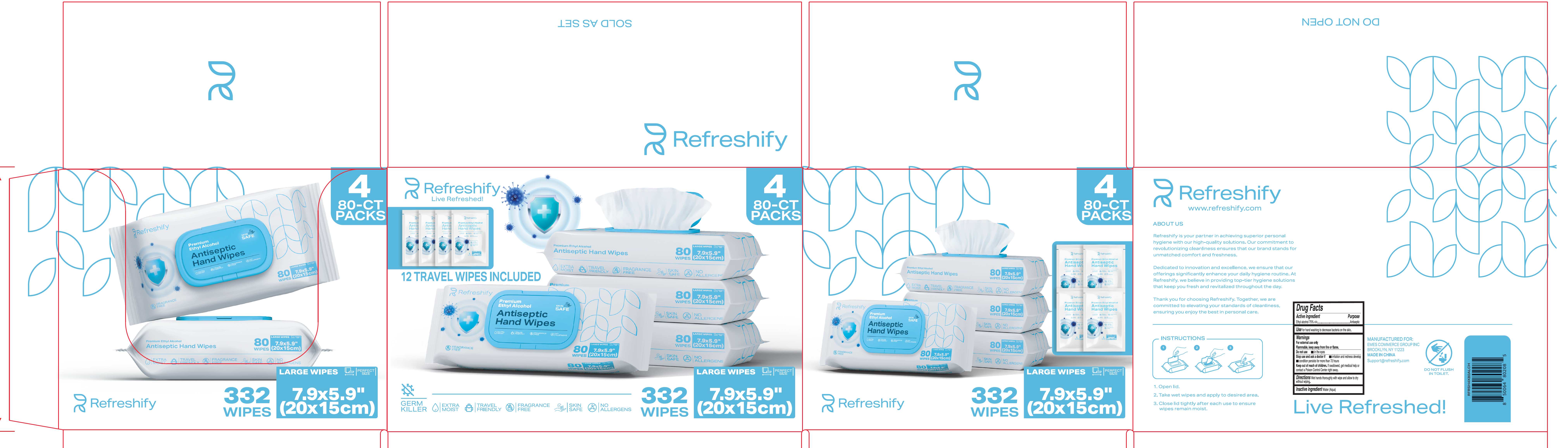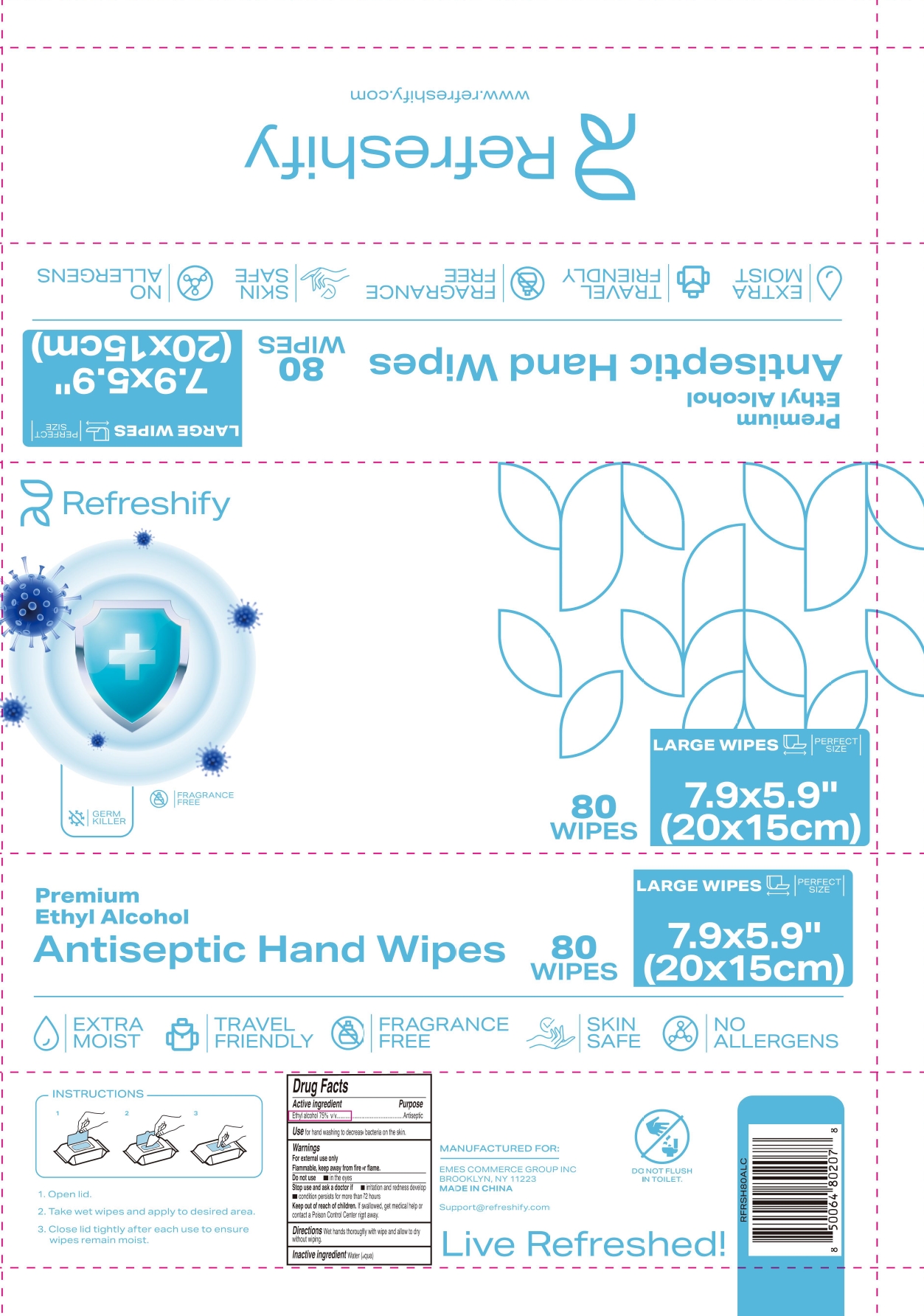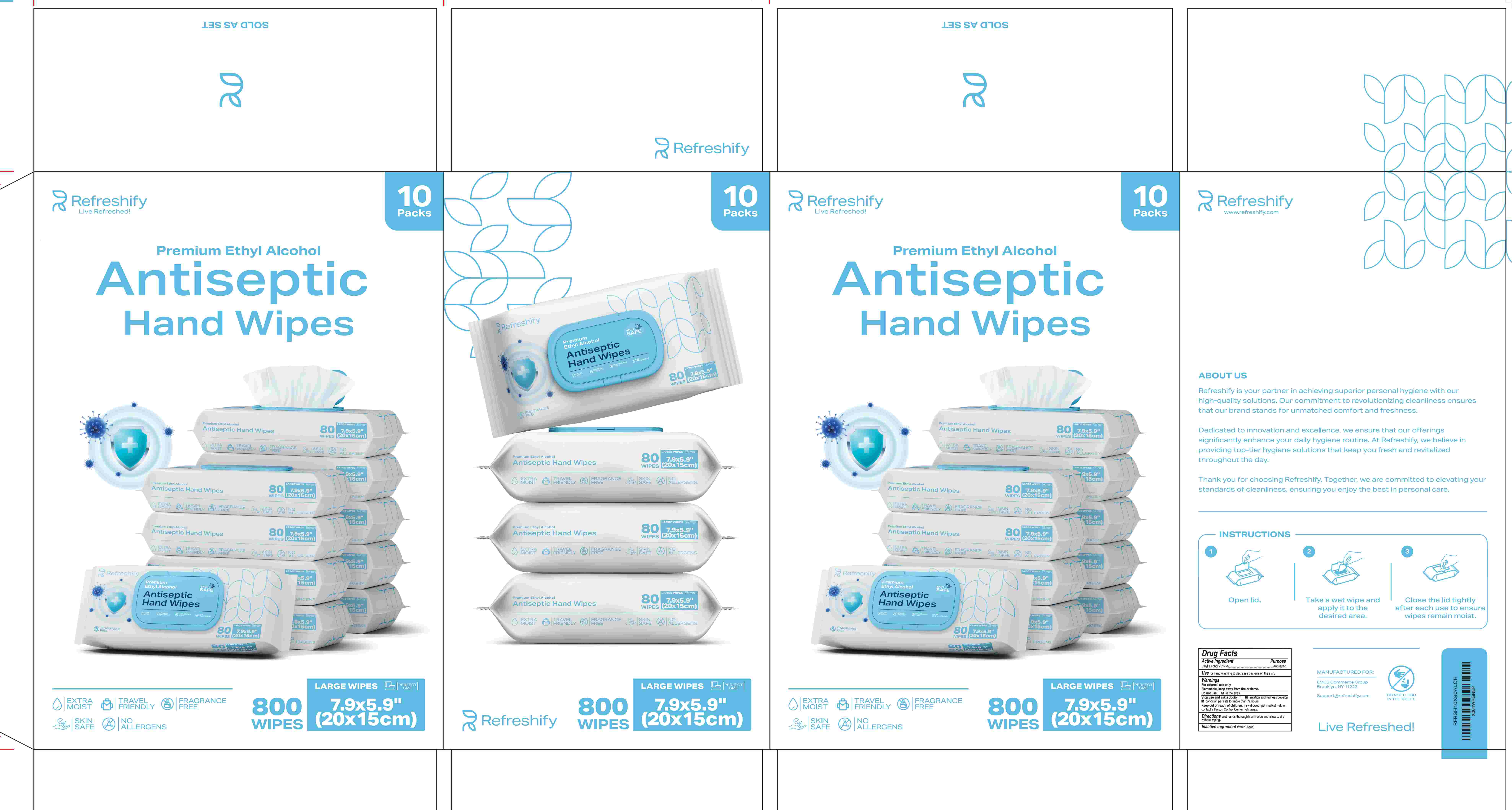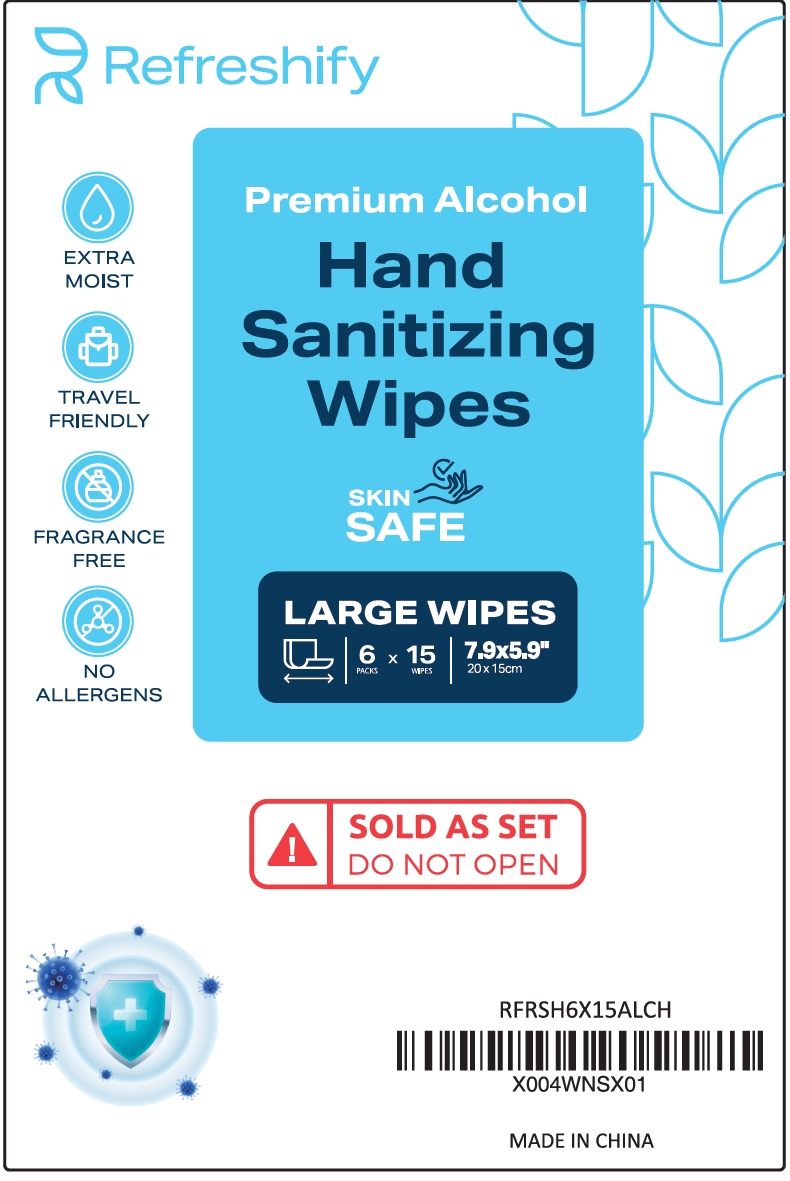 DRUG LABEL: Refreshify Antiseptic Hand Wipes
NDC: 87031-003 | Form: CLOTH
Manufacturer: Emes Commerce Group Inc.
Category: otc | Type: HUMAN OTC DRUG LABEL
Date: 20251229

ACTIVE INGREDIENTS: ALCOHOL 75 mL/100 mL
INACTIVE INGREDIENTS: WATER

87031-003 Refreshify Antiseptic Hand Wipes

ACTIVE INGREDIENT

Ethyl alcohol 75% v/v

Purpose

Antiseptic

INDICATIONS AND USAGE

Use for hand washing to decrease bacteria on the skin.

WARNINGS

For external use only
Flammable, keep away from fire or flame.

Do not use in the eyes

Stop use and ask a doctor if irritation and redness develop

condition persists for more than 72 hours

Keep out of reach of children. If swallowed, get medical help or contact a Poison Control Center right away.

DOSAGE AND ADMINISTRATION

Directions Wet hands thoroughly with wipe and allow to dry without wiping.

Inactive ingredient Water (Aqua)

PACKAGE LABEL

1
WIPE
7.9×5.9"
(20×15cm)
NDC: 87031-003-01

PACKAGE LABEL

15
Wipes
7.9×5.9"
20×15cm
NDC: 87031-003-02

PACKAGE LABEL

80
WIPES
7.9×5.9"
(20×15cm)
NDC: 87031-003-03

PACKAGE LABEL

332
WIPES
7.9×5.9"
(20×15cm)
NDC: 87031-003-04

PACKAGE LABEL

800
WIPES
7.9×5.9"
(20×15cm)
NDC: 87031-003-05

PACKAGE LABEL

90
WIPES
7.9×5.9"
(20×15cm)
NDC: 87031-003-06